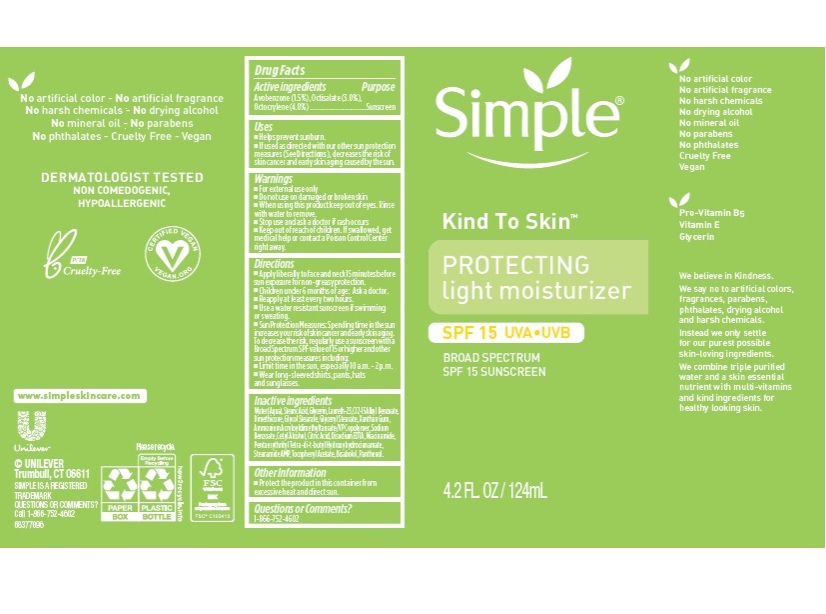 DRUG LABEL: Simple
NDC: 64942-1863 | Form: LOTION
Manufacturer: CONOPCO Inc. d/b/a Unilever
Category: otc | Type: HUMAN OTC DRUG LABEL
Date: 20241107

ACTIVE INGREDIENTS: OCTOCRYLENE 2 g/100 mL; OCTISALATE 3 g/100 mL; AVOBENZONE 1.5 g/100 mL
INACTIVE INGREDIENTS: GLYCOL STEARATE; WATER; NIACINAMIDE; GLYCERYL MONOSTEARATE; CETYL ALCOHOL; XANTHAN GUM; CITRIC ACID MONOHYDRATE; SODIUM BENZOATE; .ALPHA.-TOCOPHEROL ACETATE; DIMETHICONE; PENTAERYTHRITOL TETRAKIS(3-(3,5-DI-TERT-BUTYL-4-HYDROXYPHENYL)PROPIONATE); GLYCERIN; ALKYL (C12-15) BENZOATE; EDETATE DISODIUM ANHYDROUS; STEARAMIDE AMP; LEVOMENOL; PANTHENOL; LAURETH-23; STEARIC ACID

Simple Kind To Skin Protecting Light Moisturizer Sunscreen SPF 15

Drug Facts

Active ingredient

Avobenzone (1.5%), Octisalate (3%), Octocrylene (4%)

Purpose

Sunscreen

Uses

Help prevent sunburn
If used as directed with other sun protectionmeaseure (see Directions) decreases the risk of skin cancer and early skin aging caused by the sun

Warnings

For external use only
Do not use on damaged or broken skin
When using this product keep out of eyes. Rinse with water to remove
Stop use and ask a doctor if rash occurs

Keep out of reach of children
If product is swallowed, get medical help or contact a PoisonCcontrol Center right away.

Directions

Apply liberally to face and neck 15 minutes before sun exposure for non-greasy protection.
Children under 6 months of age: Ask a doctor.
Reapply at least every 2 hours
Use a water resistant sunscreen if swimming or sweating
Sun Protection Measures Spending time in the sun increases your risk of skin cancer and early skin aging. To decrease this rish, regularly use a sunscreen with a Broad Spectum SPF value of 15 or higher and other sun protection measures including limit time in the sun, especiallu from 10a.m. - 2p.m. wear long-sleeved shirts, pants, hats and sunglasses

Inactive ingredients

Water (Aqua), Stearic Acid, Glycerin, Laureth-23, C12-15 Alkyl Benzoate, Dimethicone, Glycol Stearate, Glyceryl Stearate, Glyceryl Stearate, Xanthan Gum, Ammonium Acryloyldimethyltaurate/VP Copolymer, Sodium Benzoate, Cetyl Alcohol, Citric Acid, Disodium EDTA, Niacinamide, Pentaerythrityl Tetra-di-t-butyl Hydroxyhydrocinnamate, Stearamide AMP, Tocopheryl Acetate, Bisabolol, Panthenol.

Questions or Comments?

1-866-752-4602